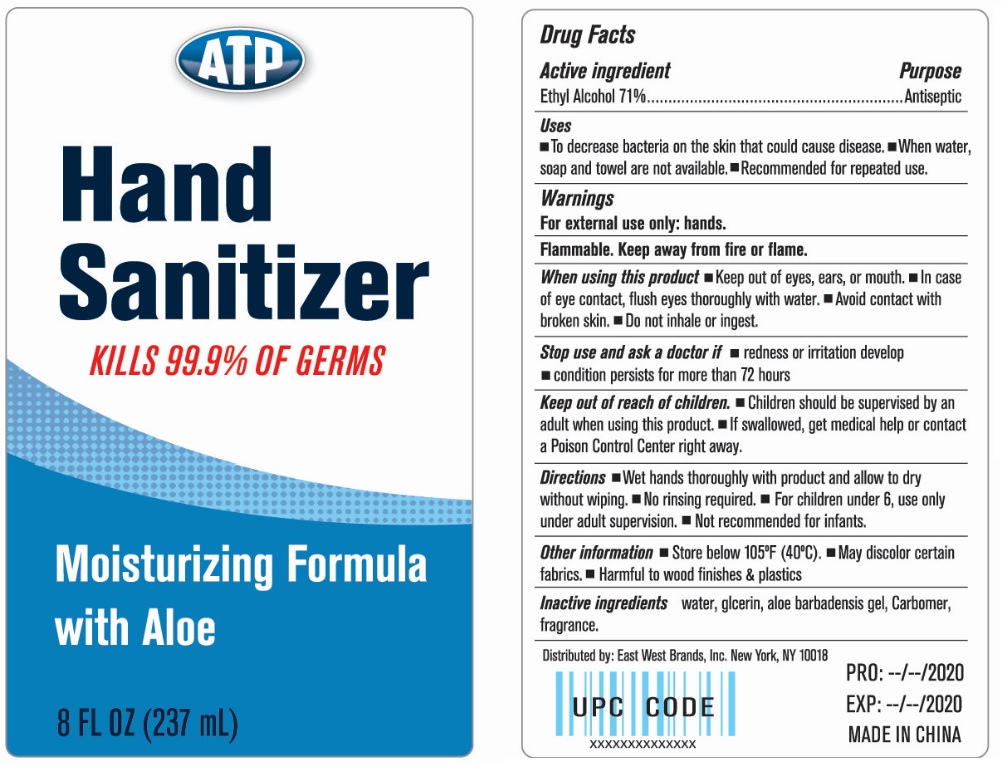 DRUG LABEL: ATP Hand Sanitizer
NDC: 73960-000 | Form: LIQUID
Manufacturer: East West Brands Inc.
Category: otc | Type: HUMAN OTC DRUG LABEL
Date: 20200409

ACTIVE INGREDIENTS: ALCOHOL 71 mL/100 mL
INACTIVE INGREDIENTS: WATER; GLYCERIN; ALOE VERA LEAF; CARBOMER HOMOPOLYMER, UNSPECIFIED TYPE

ATP Hand Sanitizer

Active ingredient

Ethyl Alcohol 71%

Purpose

Antiseptic

Uses

▪To decrease bacteria on the skin that could cause disease. ▪When water, soap and towel are not available. ▪Recommended for repeated use.

Warnings

For external use only: hands.

Flammable. Keep away from fire or flame.

When using this product ▪Keep out of eyes, ears, or mouth. ▪In case of eye contact, flush eyes thoroughly with water. ▪Avoid contact with broken skin. ▪Do not inhale or ingest.

Stop use and ask a doctor if ▪redness or irritation develop ▪condition persists for more than 72 hours

Keep out of reach of children. ▪Children should be supervised by an adult when using this product. ▪If swallowed, get medical help or contact a Poison Control Center right away.

DOSAGE AND ADMINISTRATION

Directions ▪Wet hands thoroughly with product and allow to dry without wiping. ▪No rinsing required. ▪For children under 6, use only under adult supervision. ▪Not recommended for infants.

Other information ▪Store below 105°F (40°C). ▪May discolor certain fabrics. ▪Harmful to wood finishes & plastics

INACTIVE INGREDIENT

Inactive ingredients water, glycerin, aloe barbadensis gel, Carbomer, fragrance.

KILLS 99.9% OF GERMS

Moisturizing Formula with Aloe

Distributed by: East West Brands, Inc. New York, NY 10018

MADE IN CHINA